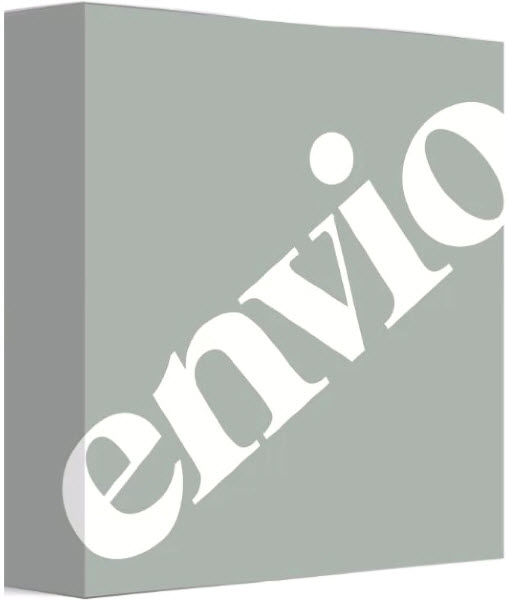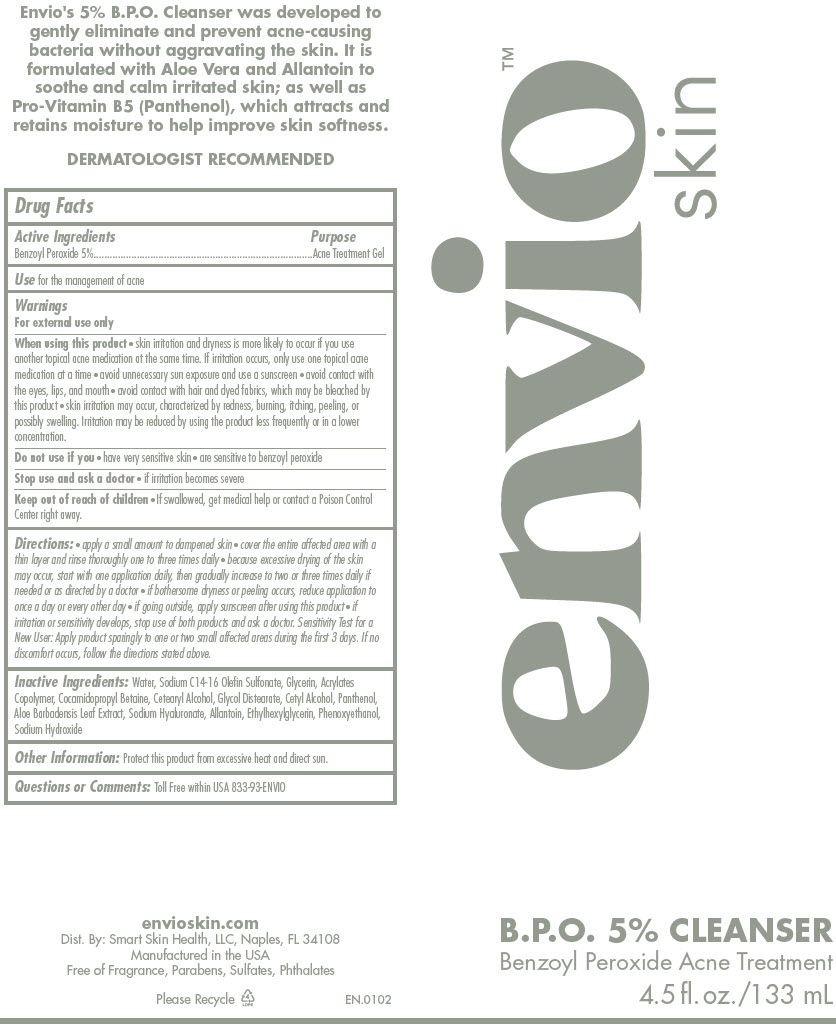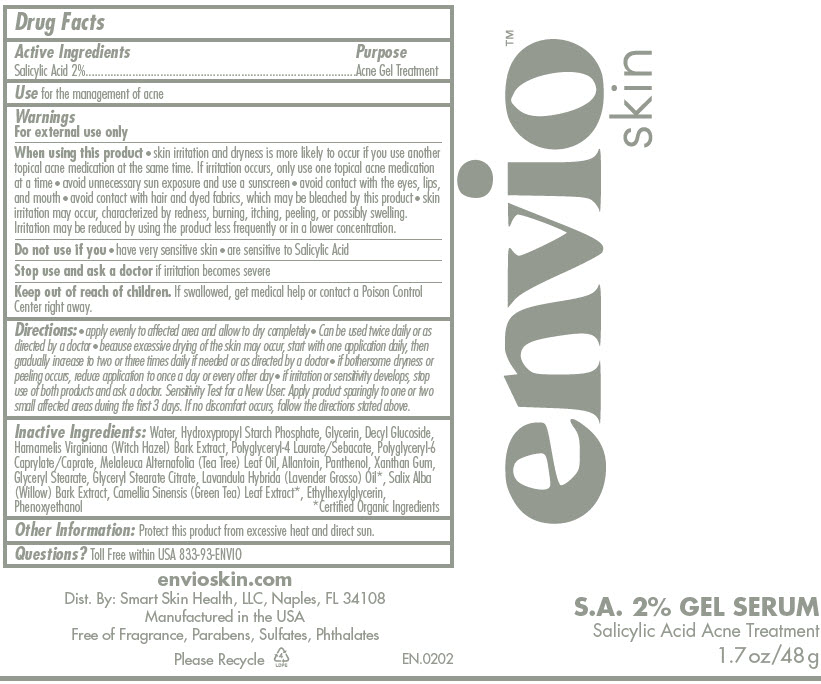 DRUG LABEL: ENVIO 90 Day Daily Essentials Trio Sub Shipment
NDC: 81252-2001 | Form: KIT | Route: TOPICAL
Manufacturer: Smart Skin Health, LLC
Category: otc | Type: HUMAN OTC DRUG LABEL
Date: 20230110

ACTIVE INGREDIENTS: Benzoyl Peroxide 5 g/100 mL; Salicylic Acid 2 g/100 g
INACTIVE INGREDIENTS: Water; Sodium C14-16 Olefin Sulfonate; Glycerin; Cocamidopropyl Betaine; Cetostearyl Alcohol; Glycol Distearate; Cetyl Alcohol; Panthenol; Aloe Vera Leaf; Hyaluronate Sodium; Allantoin; Ethylhexylglycerin; Phenoxyethanol; Sodium Hydroxide; Water; Glycerin; Decyl Glucoside; Witch Hazel; Tea Tree Oil; Allantoin; Panthenol; Xanthan Gum; Glyceryl Monostearate; Glyceryl Stearate Citrate; Ylang-Ylang Oil; Salix Alba Bark; Green Tea Leaf; Ethylhexylglycerin; Phenoxyethanol

ENVIO™ 90 Day Daily Essentials Trio Sub Shipment

B.P.O. Cleanser

Drug Facts

Active Ingredients

Benzoyl Peroxide 5%

Purpose

Acne Treatment Gel

Use

for the management of acne

Warnings

For external use only

When using this product

- skin irritation and dryness is more likely to occur if you use another topical acne medication at the same time. If irritation occurs, only use one topical acne medication at a time
- avoid unnecessary sun exposure and use a sunscreen
- avoid contact with the eyes, lips, and mouth
- avoid contact with hair and dyed fabrics, which may be bleached by this product
- skin irritation may occur, characterized by redness, burning, itching, peeling, or possibly swelling. Irritation may be reduced by using the product less frequently or in a lower concentration.

Do not use if you

- have very sensitive skin
- are sensitive to benzoyl peroxide

Stop use and ask a doctor

- if irritation becomes severe

Keep out of reach of children

- If swallowed, get medical help or contact a Poison Control Center right away.

Directions

- apply a small amount to dampened skin
- cover the entire affected area with a thin layer and rinse thoroughly one to three times daily
- because excessive drying of the skin may occur, start with one application daily, then gradually increase to two or three times daily if needed or as directed by a doctor
- if bothersome dryness or peeling occurs, reduce application to once a day or every other day
- if going outside, apply sunscreen after using this product
- if irritation or sensitivity develops, stop use of both products and ask a doctor. Sensitivity Test for a New User: Apply product sparingly to one or two small affected areas during the first 3 days. If no discomfort occurs, follow the directions stated above.

Inactive Ingredients

Water, Sodium C14-16 Olefin Sulfonate, Glycerin, Acrylates Copolymer, Cocamidopropyl Betaine, Cetearyl Alcohol, Glycol Distearate, Cetyl Alcohol, Panthenol, Aloe Barbadensis Leaf Extract, Sodium Hyaluronate, Allantoin, Ethylhexylglycerin, Phenoxyethanol, Sodium Hydroxide

Other Information

Protect this product from excessive heat and direct sun.

Questions or Comments

Toll Free within USA 833-93-ENVIO

Dist. By: Smart Skin Health, LLC, Naples, FL 34108

S.A. Serum

Drug Facts

Active Ingredients

Salicylic Acid 2%

Purpose

Acne Gel Treatment

Use

for the management of acne

Warnings

For external use only

When using this product

- skin irritation and dryness is more likely to occur if you use another topical acne medication at the same time. If irritation occurs, only use one topical acne medication at a time
- avoid unnecessary sun exposure and use a sunscreen
- avoid contact with the eyes, lips, and mouth
- avoid contact with hair and dyed fabrics, which may be bleached by this product
- skin irritation may occur, characterized by redness, burning, itching, peeling, or possibly swelling. Irritation may be reduced by using the product less frequently or in a lower concentration.

Do not use if you

- have very sensitive skin
- are sensitive to Salicylic Acid

Stop use and ask a doctor if irritation becomes severe

Keep out of reach of children. If swallowed, get medical help or contact a Poison Control Center right away.

Directions

- apply evenly to affected area and allow to dry completely
- Can be used twice daily or as directed by a doctor
- because excessive drying of the skin may occur, start with one application daily, then gradually increase to two or three times daily if needed or as directed by a doctor
- if bothersome dryness or peeling occurs, reduce application to once a day or every other day
- if irritation or sensitivity develops, stop use of both products and ask a doctor. Sensitivity Test for a New User: Apply product sparingly to one or two small affected areas during the first 3 days. If no discomfort occurs, follow the directions stated above.

Inactive Ingredients

Water, Hydroxypropyl Starch Phosphate, Glycerin, Decyl Glucoside, Hamamelis Virginiana (Witch Hazel) Bark Extract, Polyglyceryl-4 Laurate/Sebacate, Polyglyceryl-6 Caprylate/Caprate, Melaleuca Alternafolia (Tea Tree) Leaf Oil, Allantoin, Panthenol, Xanthan Gum, Glyceryl Stearate, Glyceryl Stearate Citrate, Lavandula Hybrida (Lavender Grosso) Oil [Certified Organic Ingredients] , Salix Alba (Willow) Bark Extract, Camellia Sinensis (Green Tea) Leaf Extract, Ethylhexylglycerin, Phenoxyethanol

Other Information

Protect this product from excessive heat and direct sun.

Questions?

Toll Free within USA 833-93-ENVIO

Dist. By: Smart Skin Health, LLC, Naples, FL 34108

PRINCIPAL DISPLAY PANEL - Kit Carton

envio

PRINCIPAL DISPLAY PANEL - 133 mL Tube Label

envio™
skin

B.P.O. 5% CLEANSER
Benzoyl Peroxide Acne Treatment

4.5 fl. oz. / 133 mL

PRINCIPAL DISPLAY PANEL - 48 g Tube Label

envio™
skin

S.A. 2% GEL SERUM
Salicylic Acid Acne Treatment

1.7 oz / 48 g